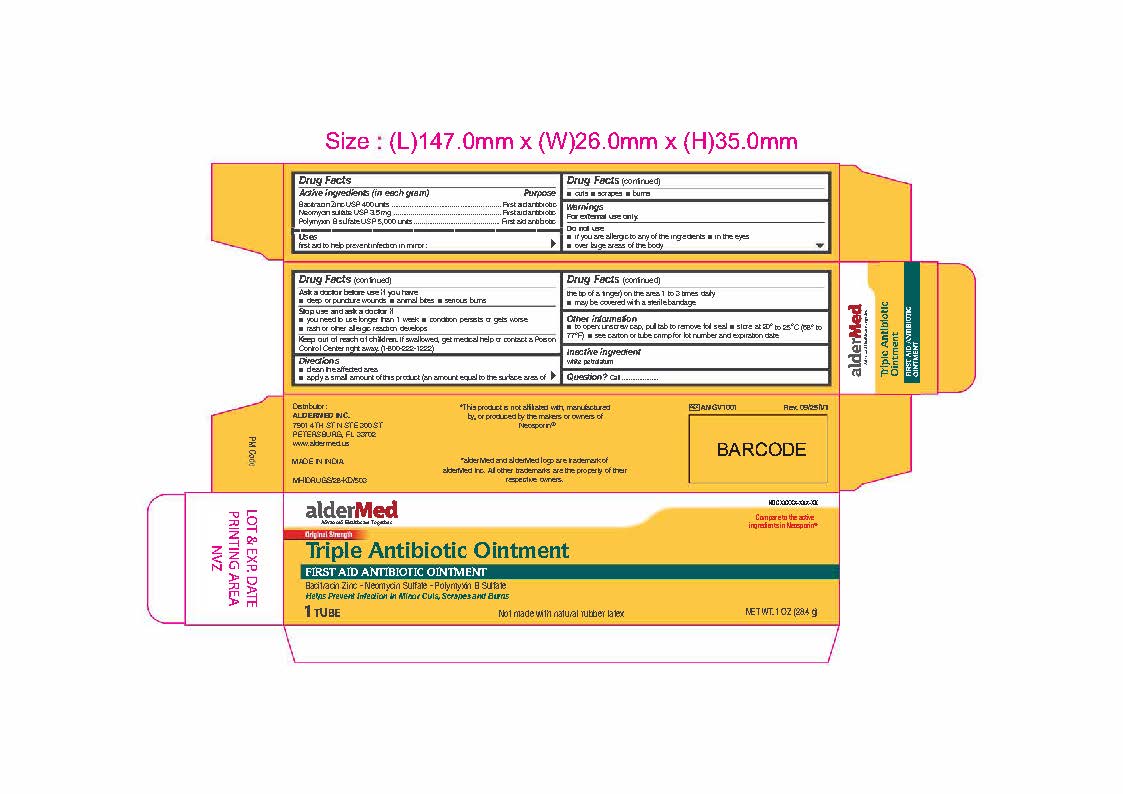 DRUG LABEL: Triple Antibiotic
NDC: 87236-002 | Form: OINTMENT
Manufacturer: Aldermed Inc.
Category: otc | Type: HUMAN OTC DRUG LABEL
Date: 20260212

ACTIVE INGREDIENTS: NEOMYCIN SULFATE 3.5 mg/1 g; BACITRACIN ZINC 400 [iU]/1 g; POLYMYXIN B SULFATE 5000 [iU]/1 g
INACTIVE INGREDIENTS: WHITE PETROLATUM

Triple Antibiotic Ointment

Drug Facts

Active ingredients

Bacitracin Zinc (400 units in each gram)

Neomycin Sulfate 5mg (equivalent to 3.5mg Neomycin per gram)

Polymyxin B Sulfate (5000 units per gram)

Purpose

First Aid Antibiotics

Uses

First Aid to help prevent infection in minor cuts, scrapes and burns

Warnings

For external use only.

Do not use

- If you are allergic to any of the ingredients
- In the eyes
- over large areas of the body

Ask a doctor before use if you have deep or puncture wounds, animal bites, or serious burns

Stop use and ask a doctor if

- you need to use longer thab 1 week
- the condition persists or gets worse
- rash or other allergic reaction develops

Keep out of reach of children. If swallowed, get medical help or contact a Poison Control Center right away (1-800-222-1222)

Directions

- Clean the affected area.
- Apply a small amount of this product (an amount equal to the surface area of the tip of a finger) on the area 1 to 3 times daily.
- May be covered with a sterile bandage.

Other information

- To open, unscrew cap, pull tab to remove foil seal.
- Store at room temperatue 20° to 25°C (68° to 77° F)
- See carton ot tube crimp for Lot Number and Expiry Date

Inactive ingredients

White Petrolatum

Questions?

Call 1-833-605-84-74 9am-5 pm EST M-F